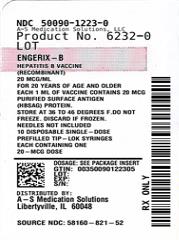 DRUG LABEL: ENGERIX-B
NDC: 50090-1223 | Form: INJECTION, SUSPENSION
Manufacturer: A-S Medication Solutions
Category: other | Type: VACCINE LABEL
Date: 20250515

ACTIVE INGREDIENTS: HEPATITIS B VIRUS SUBTYPE ADW2 HBSAG SURFACE PROTEIN ANTIGEN 20 ug/1 mL
INACTIVE INGREDIENTS: ALUMINUM HYDROXIDE; SODIUM CHLORIDE; SODIUM PHOSPHATE DIBASIC DIHYDRATE; SODIUM PHOSPHATE, MONOBASIC, DIHYDRATE

HIGHLIGHTS OF PRESCRIBING INFORMATION

These highlights do not include all the information needed to use ENGERIX-B safely and effectively. See full prescribing information for ENGERIX-B.
ENGERIX-B [Hepatitis B Vaccine (Recombinant)] injectable suspension, for intramuscular use
Initial U.S. Approval: 1989

1 INDICATIONS AND USAGE

ENGERIX-B is a vaccine indicated for immunization against infection caused by all known subtypes of hepatitis B virus. (1)

2 DOSAGE AND ADMINISTRATION

For intramuscular administration. (2, 2.2)

- Persons from birth through 19 years of age: A series of 3 doses (0.5 mL each) on a 0-, 1-, 6-month schedule. (2.3)
- Persons 20 years of age and older: A series of 3 doses (1 mL each) on a 0-, 1-, 6-month schedule. (2.3)
- Adults on hemodialysis: A series of 4 doses (2 mL each) as a single 2-mL dose or as two 1-mL doses on a 0-, 1-, 2-, 6-month schedule. (2.3)

3 DOSAGE FORMS AND STRENGTHS

ENGERIX-B is a sterile suspension available in the following presentations:

- 0.5-mL (10 mcg) prefilled syringes (3)
- 1-mL (20 mcg) single-dose vials and prefilled syringes (3)

4 CONTRAINDICATIONS

Severe allergic reaction (e.g., anaphylaxis) after a previous dose of any hepatitis B-containing vaccine, or to any component of ENGERIX-B, including yeast. (4)

5 WARNINGS AND PRECAUTIONS

- Syncope (fainting) can occur in association with administration of injectable vaccines, including ENGERIX-B. Procedures should be in place to avoid falling injury and to restore cerebral perfusion following syncope. (5.1)
- Temporarily defer vaccination of infants with a birth weight less than 2,000 g born to hepatitis B surface antigen (HBsAg)-negative mothers. (5.2)
- Apnea following intramuscular vaccination has been observed in some infants born prematurely. Decisions about when to administer an intramuscular vaccine, including ENGERIX-B, to infants born prematurely should be based on consideration of the infant’s medical status, and the potential benefits and possible risks of vaccination. (5.3)

6 ADVERSE REACTIONS

The most common solicited adverse reactions were injection-site soreness (22%) and fatigue (14%). (6.1)

To report SUSPECTED ADVERSE REACTIONS, contact GlaxoSmithKline at 1-888-825-5249 or VAERS at 1-800-822-7967 or www.vaers.hhs.gov.

7 DRUG INTERACTIONS

Do not mix ENGERIX-B with any other vaccine or product in the same syringe or vial. (7.1)

8 USE IN SPECIFIC POPULATIONS

Antibody responses are lower in persons older than 60 years than in younger adults. (8.5)

FULL PRESCRIBING INFORMATION

1 INDICATIONS AND USAGE

ENGERIX-B is indicated for immunization against infection caused by all known subtypes of hepatitis B virus.

2 DOSAGE AND ADMINISTRATION

For intramuscular administration. See Section 2.2 for subcutaneous administration in persons at risk of hemorrhage.

2.1 Preparation for Administration

Shake well before use. With thorough agitation, ENGERIX-B is a homogeneous, turbid white suspension. Do not administer if it appears otherwise. Parenteral drug products should be inspected visually for particulate matter and discoloration prior to administration, whenever solution and container permit. If either of these conditions exists, the vaccine should not be administered.

For the prefilled syringes, attach a sterile needle and administer intramuscularly.

For the vials, use a sterile needle and sterile syringe to withdraw the vaccine dose and administer intramuscularly. Changing needles between drawing vaccine from a vial and injecting it into a recipient is not necessary unless the needle has been damaged or contaminated. Use a separate sterile needle and syringe for each individual.

2.2 Administration

ENGERIX-B should be administered by intramuscular injection. The preferred administration site is the anterolateral aspect of the thigh for infants younger than 1 year and the deltoid muscle in older children (whose deltoid is large enough for an intramuscular injection) and adults. ENGERIX-B should not be administered in the gluteal region; such injections may result in suboptimal response.

ENGERIX-B may be administered subcutaneously to persons at risk of hemorrhage (e.g., hemophiliacs). However, hepatitis B vaccines administered subcutaneously are known to result in a lower antibody response. Additionally, when other aluminum-adsorbed vaccines have been administered subcutaneously, an increased incidence of local reactions including subcutaneous nodules has been observed. Therefore, subcutaneous administration should be used only in persons who are at risk of hemorrhage with intramuscular injections.

Do not administer this product intravenously or intradermally.

2.3 Recommended Dose and Schedule

Persons from Birth through 19 Years

Primary immunization for infants (born of hepatitis B surface antigen [HBsAg]-negative or HBsAg-positive mothers), children (birth through 10 years), and adolescents (aged 11 through 19 years) consists of a series of 3 doses (0.5 mL each) given on a 0-, 1-, and 6-month schedule.

Persons Aged 20 Years and Older

Primary immunization for persons aged 20 years and older consists of a series of 3 doses (1 mL each) given on a 0-, 1-, and 6-month schedule.

Adults on Hemodialysis

Primary immunization consists of a series of 4 doses (2-mL each) given as a single 2-mL dose or two 1-mL doses on a 0-, 1-, 2-, and 6-month schedule. In hemodialysis patients, antibody response is lower than in healthy persons and protection may persist only as long as antibody levels remain above 10 mIU/mL. Therefore, the need for booster doses should be assessed by annual antibody testing. A 2-mL booster dose (as a single 2-mL dose or two 1-mL doses) should be given when antibody levels decline below 10 mIU/mL.^1 [See Clinical Studies (14.2).]

Table 1. Recommended Dosage and Administration Schedules
Group | Dosea | Schedules
Infants born of:
HBsAg-negative mothers | 0.5 mL | 0, 1, 6 months
HBsAg-positive mothersb | 0.5 mL | 0, 1, 6 months
Children:
Birth through 10 years | 0.5 mL | 0, 1, 6 months
Adolescents:
Aged 11 through 19 years | 0.5 mL | 0, 1, 6 months
Adults:
Aged 20 years and older | 1 mL | 0, 1, 6 months
Adults on hemodialysis | 2 mLc | 0, 1, 2, 6 months

HBsAg = Hepatitis B surface antigen.

a 0.5 mL (10 mcg); 1 mL (20 mcg).

b Infants born to HBsAg-positive mothers should receive vaccine and hepatitis B immune globulin (HBIG) within 12 hours after birth [see Dosage and Administration (2.6)].

c Given as a single 2-mL dose or as two 1-mL doses.

2.4 Alternate Dosing Schedules

There are alternate dosing and administration schedules which may be used for specific populations (e.g., neonates born of hepatitis B–infected mothers, persons who have or might have been recently exposed to the virus, and travelers to high-risk areas) (Table 2). For some of these alternate schedules, an additional dose at 12 months is recommended for prolonged maintenance of protective titers.

Table 2. Alternate Dosage and Administration Schedules
Group | Dosea | Schedules
Infants born of:
HBsAg-positive mothersb | 0.5 mL | 0, 1, 2, 12 months
Children:
Birth through 10 years | 0.5 mL | 0, 1, 2, 12 months
Aged 5 through 10 years | 0.5 mL | 0, 12, 24 monthsc
Adolescents:
Aged 11 through 16 years | 0.5 mL | 0, 12, 24 monthsc
Aged 11 through 19 years | 1 mL | 0, 1, 6 months
Aged 11 through 19 years | 1 mL | 0, 1, 2, 12 months
Adults:
Aged 20 years and older | 1 mL | 0, 1, 2, 12 months

HBsAg = Hepatitis B surface antigen.

a 0.5 mL (10 mcg); 1 mL (20 mcg).

b Infants born to HBsAg-positive mothers should receive vaccine and hepatitis B immune globulin (HBIG) within 12 hours after birth [see Dosage and Administration (2.6)].

c For children and adolescents for whom an extended administration schedule is acceptable based on risk of exposure.

2.5 Booster Vaccinations

Whenever administration of a booster dose is appropriate, the dose of ENGERIX-B is 0.5 mL for children aged 10 years and younger and 1 mL for persons aged 11 years and older. Studies have demonstrated a substantial increase in antibody titers after booster vaccination with ENGERIX-B. See Section 2.3 for information on booster vaccination for adults on hemodialysis.

2.6 Known or Presumed Exposure to Hepatitis B Virus

Persons with known or presumed exposure to the hepatitis B virus (e.g., neonates born of infected mothers, persons who experienced percutaneous or permucosal exposure to the virus) should be given hepatitis B immune globulin (HBIG) in addition to ENGERIX-B in accordance with Advisory Committee on Immunization Practices recommendations and with the package insert for HBIG. ENGERIX-B can be given on either dosing schedule (0, 1, and 6 months or 0, 1, 2, and 12 months).

3 DOSAGE FORMS AND STRENGTHS

ENGERIX-B is a sterile suspension available in the following presentations:

- 0.5-mL (10 mcg) prefilled TIP-LOK syringes
- 1-mL (20 mcg) single-dose vials and prefilled TIP-LOK syringes

[See Description (11), How Supplied/Storage and Handling (16).]

4 CONTRAINDICATIONS

Severe allergic reaction (e.g., anaphylaxis) after a previous dose of any hepatitis B-containing vaccine, or to any component of ENGERIX-B, including yeast, is a contraindication to administration of ENGERIX-B [see Description (11)].

5 WARNINGS AND PRECAUTIONS

5.1 Syncope

Syncope (fainting) can occur in association with administration of injectable vaccines, including ENGERIX-B. Syncope can be accompanied by transient neurological signs such as visual disturbance, paresthesia, and tonic-clonic limb movements. Procedures should be in place to avoid falling injury and to restore cerebral perfusion following syncope.

5.2 Infants Weighing Less than 2,000 g at Birth

Hepatitis B vaccine should be deferred for infants with a birth weight <2,000 g if the mother is documented to be HBsAg negative at the time of the infant’s birth. Vaccination can commence at chronological age 1 month or hospital discharge. Infants born weighing <2,000 g to HBsAg-positive mothers should receive vaccine and HBIG within 12 hours after birth. Infants born weighing <2,000 g to mothers of unknown HBsAg status should receive vaccine and HBIG within 12 hours after birth if the mother’s HBsAg status cannot be determined within the first 12 hours of life. The birth dose in infants born weighing <2,000 g should not be counted as the first dose in the vaccine series and it should be followed with a full 3-dose standard regimen (total of 4 doses).^2 [See Dosage and Administration (2).]

5.3 Apnea in Premature Infants

Apnea following intramuscular vaccination has been observed in some infants born prematurely. Decisions about when to administer an intramuscular vaccine, including ENGERIX-B, to infants born prematurely should be based on consideration of the infant’s medical status, and the potential benefits and possible risks of vaccination. For ENGERIX-B, this assessment should include consideration of the mother’s hepatitis B antigen status and the high probability of maternal transmission of hepatitis B virus to infants born of mothers who are HBsAg positive if vaccination is delayed.

5.4 Preventing and Managing Allergic Vaccine Reactions

Prior to immunization, the healthcare provider should review the immunization history for possible vaccine sensitivity and previous vaccination-related adverse reactions to allow an assessment of benefits and risks. Epinephrine and other appropriate agents used for the control of immediate allergic reactions must be immediately available should an acute anaphylactic reaction occur. [See Contraindications (4).]

5.5 Moderate or Severe Acute Illness

To avoid diagnostic confusion between manifestations of an acute illness and possible vaccine adverse effects, vaccination with ENGERIX-B should be postponed in persons with moderate or severe acute febrile illness unless they are at immediate risk of hepatitis B infection (e.g., infants born of HBsAg-positive mothers).

5.6 Altered Immunocompetence

Immunocompromised persons may have a diminished immune response to ENGERIX-B, including individuals receiving immunosuppressant therapy.

5.7 Multiple Sclerosis

Results from 2 clinical studies indicate that there is no association between hepatitis B vaccination and the development of multiple sclerosis,^3 and that vaccination with hepatitis B vaccine does not appear to increase the short‑term risk of relapse in multiple sclerosis.^4

5.8 Limitations of Vaccine Effectiveness

Hepatitis B has a long incubation period. ENGERIX-B may not prevent hepatitis B infection in individuals who had an unrecognized hepatitis B infection at the time of vaccine administration. Additionally, it may not prevent infection in individuals who do not achieve protective antibody titers.

6 ADVERSE REACTIONS

6.1 Clinical Trials Experience

Because clinical trials are conducted under widely varying conditions, adverse reaction rates observed in the clinical trials of a vaccine cannot be directly compared with rates in the clinical trials of another vaccine and may not reflect the rates observed in practice.

The most common solicited adverse reactions were injection site soreness (22%) and fatigue (14%).

In 36 clinical studies, a total of 13,495 doses of ENGERIX-B were administered to 5,071 healthy adults and children who were initially seronegative for hepatitis B markers, and healthy neonates. All subjects were monitored for 4 days post-administration. Frequency of adverse reactions tended to decrease with successive doses of ENGERIX-B.

Using a symptom checklist, the most frequently reported adverse reactions were injection site soreness (22%) and fatigue (14%). Other reactions are listed below. Parent or guardian completed forms for children and neonates. Neonatal checklist did not include headache, fatigue, or dizziness.

Incidence 1% to 10% of Injections

Nervous System Disorders: Dizziness, headache.

General Disorders and Administration Site Conditions: Fever (>37.5°C), injection site erythema, injection site induration, injection site swelling.

Incidence <1% of Injections

Infections and Infestations: Upper respiratory tract illnesses.

Blood and Lymphatic System Disorders: Lymphadenopathy.

Metabolism and Nutrition Disorders: Anorexia.

Psychiatric Disorders: Agitation, insomnia.

Nervous System Disorders: Somnolence, tingling.

Vascular Disorders: Flushing, hypotension.

Gastrointestinal Disorders: Abdominal pain/cramps, constipation, diarrhea, nausea, vomiting.

Skin and Subcutaneous Tissue Disorders: Erythema, petechiae, pruritus, rash, sweating, urticaria.

Musculoskeletal and Connective Tissue Disorders: Arthralgia, back pain, myalgia, pain/stiffness in arm, shoulder, or neck.

General Disorders and Administration Site Conditions: Chills, influenza-like symptoms, injection site ecchymosis, injection site pain, injection site pruritus, irritability, malaise, weakness.

In a clinical trial, 416 adults with type 2 diabetes and 258 control subjects without type 2 diabetes who were seronegative for hepatitis B markers received at least 1 dose of ENGERIX-B. Subjects were monitored for solicited adverse reactions for 4 days following each vaccination. The most frequently reported solicited adverse reactions in the entire study population were injection site pain (reported in 39% of diabetic subjects and 45% of control subjects) and fatigue (reported in 29% of diabetic subjects and 27% of control subjects). Serious adverse events were monitored through 30 days following the last vaccination. Serious adverse events (SAEs) occurred in 3.8% of diabetic subjects and 1.6% of controls. No SAEs were deemed related to ENGERIX-B.

6.2 Postmarketing Experience

The following adverse reactions have been identified during post-approval use of ENGERIX-B. Because these reactions are reported voluntarily from a population of uncertain size, it is not always possible to reliably estimate their frequency or establish a causal relationship to the vaccine.

Infections and Infestations

Herpes zoster, meningitis.

Blood and Lymphatic System Disorders

Thrombocytopenia.

Immune System Disorders

Allergic reaction, anaphylactoid reaction, anaphylaxis. An apparent hypersensitivity syndrome (serum sickness-like) of delayed onset has been reported days to weeks after vaccination, including: arthralgia/arthritis (usually transient), fever, and dermatologic reactions such as urticaria, erythema multiforme, ecchymoses, and erythema nodosum.

Nervous System Disorders

Encephalitis; encephalopathy; migraine; multiple sclerosis; neuritis; neuropathy including hypoesthesia, paresthesia, Guillain-Barré syndrome and Bell’s palsy; optic neuritis; paralysis; paresis; seizures; syncope; transverse myelitis.

Eye Disorders

Conjunctivitis, keratitis, visual disturbances.

Ear and Labyrinth Disorders

Earache, tinnitus, vertigo.

Cardiac Disorders

Palpitations, tachycardia.

Vascular Disorders

Vasculitis.

Respiratory, Thoracic, and Mediastinal Disorders

Apnea, bronchospasm including asthma-like symptoms.

Gastrointestinal Disorders

Dyspepsia.

Skin and Subcutaneous Tissue Disorders

Alopecia, angioedema, eczema, erythema multiforme including Stevens-Johnson syndrome, erythema nodosum, lichen planus, purpura.

Musculoskeletal and Connective Tissue Disorders

Arthritis, muscular weakness.

General Disorders and Administration Site Conditions

Injection site reaction.

Investigations

Abnormal liver function tests.

7 DRUG INTERACTIONS

7.1 Concomitant Administration with Vaccines and Immune Globulin

ENGERIX-B may be administered concomitantly with immune globulin.

When concomitant administration of other vaccines or immune globulin is required, they should be given with different syringes and at different injection sites. Do not mix ENGERIX-B with any other vaccine or product in the same syringe or vial.

7.2 Interference with Laboratory Tests

HBsAg derived from hepatitis B vaccines has been transiently detected in blood samples following vaccination. Serum HBsAg detection may not have diagnostic value within 28 days after receipt of a hepatitis B vaccine, including ENGERIX-B.

8 USE IN SPECIFIC POPULATIONS

8.1 Pregnancy

Risk Summary

All pregnancies have a risk of birth defect, loss, or other adverse outcomes. In the U.S. general population, the estimated background risk of major birth defects and miscarriage in clinically recognized pregnancies is 2% to 4% and 15% to 20%, respectively.

There are no adequate and well-controlled studies of ENGERIX-B in pregnant women in the U.S. Available data do not suggest an increased risk of major birth defects and miscarriage in women who received ENGERIX-B during pregnancy (see Data).

There are no animal studies with ENGERIX-B to inform use during pregnancy. A developmental toxicity study was performed in female rats administered a vaccine with the same hepatitis B surface antigen component and quantity as ENGERIX-B prior to mating and during gestation (0.2 mL at each occasion). This study revealed no adverse effects on fetal or pre-weaning development (see Data).

Data

Human Data: In an evaluation of pre- and post-licensure clinical trials of ENGERIX-B, 58 pregnant women were inadvertently administered ENGERIX-B following their last menstrual period. After excluding elective terminations (n = 6), those with an unknown outcome (n = 3), those with exposure in the third trimester (n = 1), and those with an unknown exposure timing (n = 22), there were 26 pregnancies with known outcomes with exposure in the first or second trimester. Miscarriage was reported in 11.5% of pregnancies with exposure prior to 20 weeks of gestation (3/26) and major birth defects were reported in 0% (0/23) of live births born to women with exposure during the first or second trimester. The rates of miscarriage and major birth defects were consistent with estimated background rates.

No pregnancy registry for ENGERIX-B was conducted. TWINRIX [Hepatitis A & Hepatitis B (Recombinant) Vaccine] is a bivalent vaccine containing the same hepatitis B surface antigen component and quantity as used in ENGERIX-B. Therefore, clinical data accrued with TWINRIX are relevant to ENGERIX-B. A pregnancy exposure registry was maintained for TWINRIX from 2001 to 2015. The registry prospectively enrolled 245 women who received a dose of TWINRIX during pregnancy or within 28 days prior to conception. After excluding induced abortions (n = 6, including one of a fetus with congenital anomalies), those lost to follow-up (n = 142), those with exposure in the third trimester (n = 1), and those with an unknown exposure timing (n = 9), there were 87 pregnancies with known outcomes with exposure within 28 days prior to conception, or in the first or second trimesters. Miscarriage was reported for 9.6% of pregnancies with exposure to TWINRIX prior to 20 weeks gestation (8/83). Major birth defects were reported for 3.8% of live born infants whose mothers were exposed within 28 days prior to conception or during the first or second trimester (3/80). The rates of miscarriage and major birth defects were consistent with estimated background rates.

Animal Data: In a developmental toxicity study, female rats were administered TWINRIX, which contains the same hepatitis B surface antigen component and quantity as ENGERIX-B, by intramuscular injection on Day 30 prior to mating and on gestation Days 6, 8, 11, and 15. The total dose was 0.2 mL (divided) at each occasion (a single human dose is 1 mL). No adverse effects on pre-weaning development up to post-natal Day 25 were observed. There were no fetal malformations or variations.

8.2 Lactation

Risk Summary

There is no information regarding the presence of ENGERIX-B in human milk, the effects on the breastfed child, or the effects on milk production. The developmental and health benefits of breastfeeding should be considered along with the mother’s clinical need for ENGERIX-B and any potential adverse effects on the breastfed child from ENGERIX-B or from the underlying maternal condition. For preventive vaccines, the underlying maternal condition is susceptibility to disease prevented by the vaccine.

8.4 Pediatric Use

Safety and effectiveness of ENGERIX-B have been established in all pediatric age-groups. Maternally transferred antibodies do not interfere with the active immune response to the vaccine. [See Adverse Reactions (6), Clinical Studies (14.1, 14.3, 14.4).]

The timing of the first dose in infants weighing less than 2,000 g at birth depends on the HBsAg status of the mother. [See Warnings and Precautions (5.2).]

8.5 Geriatric Use

Clinical studies of ENGERIX-B used for licensure did not include sufficient numbers of subjects aged 65 years and older to determine whether they respond differently from younger subjects. However, in later studies it has been shown that a diminished antibody response and seroprotective levels can be expected in persons older than 60 years.^5 [See Clinical Studies (14.2).]

11 DESCRIPTION

ENGERIX-B [Hepatitis B Vaccine (Recombinant)] is a sterile suspension of noninfectious HBsAg for intramuscular administration. It contains purified surface antigen of the virus obtained by culturing genetically engineered Saccharomyces cerevisiae cells, which carry the surface antigen gene of the hepatitis B virus. The HBsAg expressed in the cells is purified by several physicochemical steps and formulated as a suspension of the antigen adsorbed on aluminum hydroxide. The procedures used to manufacture ENGERIX-B result in a product that contains no more than 5% yeast protein.

Each 0.5-mL pediatric/adolescent dose contains 10 mcg of HBsAg adsorbed on 0.25 mg aluminum as aluminum hydroxide.

Each 1-mL adult dose contains 20 mcg of HBsAg adsorbed on 0.5 mg aluminum as aluminum hydroxide.

ENGERIX-B contains the following excipients: Sodium chloride (8 mg/mL) and phosphate buffers (disodium phosphate dihydrate, 0.9 mg/mL; sodium dihydrogen phosphate dihydrate, 0.7 mg/mL).

ENGERIX‑B is available in vials (adult dose only) and prefilled syringes. The tip cap and rubber plunger stopper of the prefilled syringe are not made with natural rubber latex. The vial stoppers are not made with natural rubber latex.

ENGERIX-B is formulated without preservatives.

12 CLINICAL PHARMACOLOGY

12.1 Mechanism of Action

Infection with hepatitis B virus can have serious consequences including acute massive hepatic necrosis and chronic active hepatitis. Chronically infected persons are at increased risk for cirrhosis and hepatocellular carcinoma.

Antibody concentrations ≥10 mIU/mL against HBsAg are recognized as conferring protection against hepatitis B virus infection.^1 Seroconversion is defined as antibody titers ≥1 mIU/mL.

13 NONCLINICAL TOXICOLOGY

13.1 Carcinogenesis, Mutagenesis, Impairment of Fertility

ENGERIX‑B has not been evaluated for carcinogenic or mutagenic potential, or for impairment of male fertility in animals. Vaccination of female rats with TWINRIX, which contains the same HBsAg component and quantity as ENGERIX-B, had no effect on fertility. [See Use in Specific Populations (8.1).]

14 CLINICAL STUDIES

14.1 Efficacy in Neonates

Protective efficacy with ENGERIX-B has been demonstrated in a clinical trial in neonates at high risk of hepatitis B infection.^6,7 Fifty-eight neonates born of mothers who were both HBsAg-positive and hepatitis B “e” antigen (HBeAg)-positive were given ENGERIX-B (10 mcg/0.5 mL) at 0, 1, and 2 months, without concomitant hepatitis B immune globulin (HBIG). Two infants became chronic carriers in the 12-month follow-up period after initial inoculation. Assuming an expected carrier rate of 70%, the protective efficacy rate against the chronic carrier state during the first 12 months of life was 95%.

14.2 Efficacy and Immunogenicity in Specific Populations

Homosexual Men

ENGERIX-B (20 mcg/1 mL) given at 0, 1, and 6 months was evaluated in homosexual men aged 16 to 59 years. Four of 244 subjects became infected with hepatitis B during the period prior to completion of the 3-dose immunization schedule. No additional subjects became infected during the 18-month follow-up period after completion of the immunization course.

Adults with Chronic Hepatitis C

In a clinical trial of 67 adults aged 25 to 67 years with chronic hepatitis C, ENGERIX-B (20 mcg/1 mL) was given at 0, 1, and 6 months. Of the subjects assessed at Month 7 (n = 31), 100% responded with seroprotective titers. The geometric mean antibody titer (GMT) was 1,260 mIU/mL (95% Confidence Interval [CI]: 709, 2,237).

Adults on Hemodialysis

Hemodialysis patients given hepatitis B vaccines respond with lower titers, which remain at protective levels for shorter durations than in normal subjects. In a clinical trial of 56 adults who had been on hemodialysis for a mean period of 56 months, ENGERIX-B (40 mcg/2 mL given as two 1-mL doses) was given at 0, 1, 2, and 6 months. Two months after the fourth dose, 67% (29/43) of patients had seroprotective antibody levels (≥10 mIU/mL) and the GMT among seroconverters was 93 mIU/mL.

Adults with Type 2 Diabetes Mellitus

In a descriptive study, 674 adult subjects with type 2 diabetes (diagnosed within the preceding 5 years) or without type 2 diabetes were enrolled and stratified by age and body mass index (BMI). The per-protocol immunogenicity cohort included 378 diabetic subjects and 189 matched control subjects who received ENGERIX-B (20 mcg/1 mL) at 0, 1, and 6 months. Among these subjects, the mean age was 54 years (range: 20 to 82 years); mean BMI was 32 kg/m^2 (range: 17 to 64 kg/m^2); 51% were male; 88% were white, 3% were American Indian or Alaskan Native, 3% were black, 2% were Asian, 4% were other racial groups; 2% were Hispanic or Latino.

The overall seroprotection rates (1 month after the third dose) were 75% (95% CI: 71, 80) in patients with diabetes and 82% (95% CI: 76, 87) in control subjects. The seroprotection rates in those with diabetes aged 20 to 39 years, 40 to 49 years, 50 to 59 years, and at least 60 years were 89%, 81%, 83%, and 58%, respectively. The seroprotection rates in those without diabetes in these same age-groups were 100%, 86%, 82%, and 70%, respectively. Subjects with diabetes and a BMI of at least 30 kg/m^2 had a seroprotection rate of 72% compared with 80% in diabetic subjects with lower BMIs. In control subjects, seroprotection rates were 82% in those with a BMI of at least 30 kg/m^2 and 83% in those with lower BMIs.

14.3 Immunogenicity in Neonates

In clinical studies, neonates were given ENGERIX-B (10 mcg/0.5 mL) at age 0, 1, and 6 months or at age 0, 1, and 2 months. The immune response to vaccination was evaluated in sera obtained 1 month after the third dose of ENGERIX-B.

Among infants administered ENGERIX-B at age 0, 1, and 6 months, 100% of evaluable subjects (n = 52) seroconverted by Month 7. The GMT was 713 mIU/mL. Of these, 97% had seroprotective levels (≥10 mIU/mL).

Among infants enrolled (n = 381) to receive ENGERIX-B at age 0, 1, and 2 months, 96% had seroprotective levels (≥10 mIU/mL) by Month 4. The GMT among seroconverters (n = 311) (antibody titer ≥1 mIU/mL) was 210 mIU/mL. A subset of these children received a fourth dose of ENGERIX-B at age 12 months. One month following this dose, seroconverters (n = 126) had a GMT of 2,941 mIU/mL.

14.4 Immunogenicity in Children and Adults

Persons Aged 6 Months through 10 Years

In clinical trials, children (N = 242) aged 6 months through 10 years were given ENGERIX-B (10 mcg/0.5 mL) at 0, 1, and 6 months. One to 2 months after the third dose, the seroprotection rate was 98% and the GMT of seroconverters was 4,023 mIU/mL.

Persons Aged 5 through 16 Years

In a separate clinical trial including both children and adolescents aged 5 through 16 years, ENGERIX-B (10 mcg/0.5 mL) was administered at 0, 1, and 6 months (n = 181) or 0, 12, and 24 months (n = 161). Immediately before the third dose of vaccine, seroprotection was achieved in 92.3% of subjects vaccinated on the 0-, 1-, and 6-month schedule and 88.8% of subjects on the 0-, 12-, and 24-month schedule (GMT: 118 mIU/mL versus 162 mIU/mL, respectively, P = 0.18). One month following the third dose, seroprotection was achieved in 99.5% of children vaccinated on the 0-, 1-, and 6-month schedule compared with 98.1% of those on the 0-, 12-, and 24-month schedule. GMTs were higher (P = 0.02) for children receiving vaccine on the 0-, 1-, and 6-month schedule compared with those on the 0-, 12-, and 24-month schedule (5,687 mIU/mL versus 3,159 mIU/mL, respectively).

Persons Aged 11 through 19 Years

In clinical trials with healthy adolescent subjects aged 11 through 19 years, ENGERIX-B (10 mcg/0.5 mL) given at 0, 1, and 6 months produced a seroprotection rate of 97% at Month 8 (n = 119) with a GMT of 1,989 mIU/mL (n = 118, 95% CI: 1,318, 3,020). Immunization with ENGERIX-B (20 mcg/1 mL) at 0, 1, and 6 months produced a seroprotection rate of 99% at Month 8 (n = 122) with a GMT of 7,672 mIU/mL (n = 122, 95% CI: 5,248, 10,965).

Persons Aged 16 through 65 Years

Clinical trials in healthy adult and adolescent subjects (aged 16 through 65 years) have shown that following a course of 3 doses of ENGERIX-B (20 mcg/1 mL) given at 0, 1, and 6 months, the seroprotection (antibody titers ≥10 mIU/mL) rate for all individuals was 79% at Month 6 (5 months after second dose) and 96% at Month 7 (1 month after third dose); the GMT for seroconverters was 2,204 mIU/mL at Month 7 (n = 110).

An alternate 3-dose schedule (20 mcg/1 mL given at 0, 1, and 2 months) designed for certain populations (e.g., individuals who have or might have been recently exposed to the virus and travelers to high-risk areas) was also evaluated. At Month 3 (1 month after third dose), 99% of all individuals were seroprotected and remained protected through Month 12. On the alternate schedule, a fourth dose of ENGERIX-B (20 mcg/1 mL) at 12 months produced a GMT of 9,163 mIU/mL at Month 13 (1 month after fourth dose) (n = 373).

Persons Aged 40 Years and Older

Among subjects aged 40 years and older given ENGERIX-B (20 mcg/1 mL) at 0, 1, and 6 months, the seroprotection rate 1 month after the third dose was 88% and the GMT for seroconverters was 610 mIU/mL (n = 50). In adults aged older than 40 years, ENGERIX-B produced anti-HBsAg antibody titers that were lower than those in younger adults.

14.5 Interchangeability with Other Hepatitis B Vaccines

A controlled study (N = 48) demonstrated that completion of a course of immunization with 1 dose of ENGERIX-B (20 mcg/1 mL) at Month 6 following 2 doses of RECOMBIVAX HB [Hepatitis B Vaccine (Recombinant)] (10 mcg) at Months 0 and 1 produced a similar GMT (4,077 mIU/mL) to immunization with 3 doses of RECOMBIVAX HB (10 mcg) at Months 0, 1, and 6 (GMT: 2,654 mIU/mL). Thus, ENGERIX-B can be used to complete a vaccination course initiated with RECOMBIVAX HB.^8

15 REFERENCES

1. Centers for Disease Control and Prevention. Hepatitis B. In: Atkinson W, Wolfe C, Humiston S, Nelson R, eds. Epidemiology and Prevention of Vaccine-Preventable Diseases. 6th ed. Atlanta, GA: Public Health Foundation; 2000:207-229.
2. Centers for Disease Control and Prevention. A Comprehensive Immunization Strategy to Eliminate Transmission of Hepatitis B Virus Infection in the United States. Recommendations of the Advisory Committee on Immunization Practices (ACIP). Part 1: Immunization of Infants, Children, and Adolescents, MMWR. 2005;54(RR-16):1-23.
3. Ascherio A, Zhang SM, Hernán MA, et al. Hepatitis B vaccination and the risk of multiple sclerosis. N Engl J Med. 2001;344(5):327-332.
4. Confavreux C, Suissa S, Saddier P, et al. Vaccination and the risk of relapse in multiple sclerosis. N Engl J Med. 2001-344(5):319-326.
5. Centers for Disease Control and Prevention. A Comprehensive Immunization Strategy to Eliminate Transmission of Hepatitis B Virus Infection in the United States. Recommendations of the Advisory Committee on Immunization Practices (ACIP). Part 2: Immunization of Adults, MMWR. 2006;55(RR-16):1-25.
6. André FE, Safary A. Clinical experience with a yeast-derived hepatitis B vaccine. In: Zuckerman AJ, ed. Viral Hepatitis and Liver Disease. New York, NY: Alan R Liss, Inc.; 1988:1025-1030.
7. Poovorawan Y, Sanpavat S, Pongpunlert W, et al. Protective efficacy of a recombinant DNA hepatitis B vaccine in neonates of HBe antigen-positive mothers. JAMA. 1989;261(22):3278-3281.
8. Bush LM, Moonsammy GI, Boscia JA. Evaluation of initiating a hepatitis B vaccination schedule with one vaccine and completing it with another. Vaccine. 1991;9(11):807-809.

16 HOW SUPPLIED/STORAGE AND HANDLING

Product: 50090-1223

NDC: 50090-1223-1 1 mL in a VIAL, SINGLE-DOSE / 1 in a POUCH

NDC: 50090-1223-0 1 mL in a VIAL, SINGLE-DOSE / 10 in a CARTON

17 PATIENT COUNSELING INFORMATION

- Inform vaccine recipients and parents or guardians of the potential benefits and risks of immunization with ENGERIX-B.
- Emphasize, when educating vaccine recipients and parents or guardians regarding potential side effects, that ENGERIX-B contains non-infectious purified HBsAg and cannot cause hepatitis B infection.
- Instruct vaccine recipients and parents or guardians to report any adverse events to their healthcare provider.
- Give vaccine recipients and parents or guardians the Vaccine Information Statements, which are required by the National Childhood Vaccine Injury Act of 1986 to be given prior to immunization. These materials are available free of charge at the Centers for Disease Control and Prevention (CDC) website (www.cdc.gov/vaccines).

ENGERIX-B, TWINRIX, and TIP-LOK are trademarks owned by or licensed to the GSK group of companies. The other brand listed is a trademark owned by or licensed to the respective owner and is not owned by or licensed to the GSK group of companies. The maker of this brand is not affiliated with and does not endorse the GSK group of companies or its products.

Manufactured by GlaxoSmithKline Biologicals

Rixensart, Belgium, U.S. License No. 1617

Distributed by GlaxoSmithKline

Durham, NC 27701

©2024 GSK group of companies or its licensor.

ENG:62PI